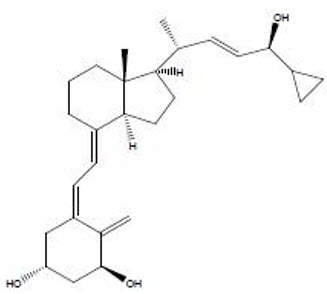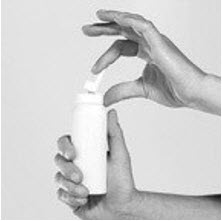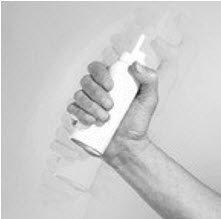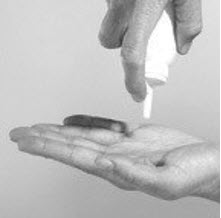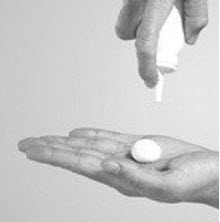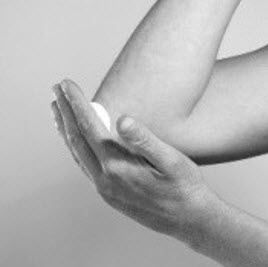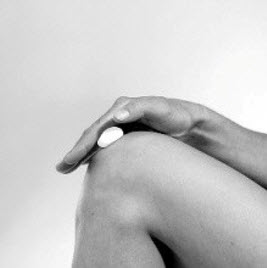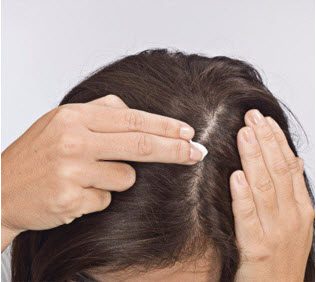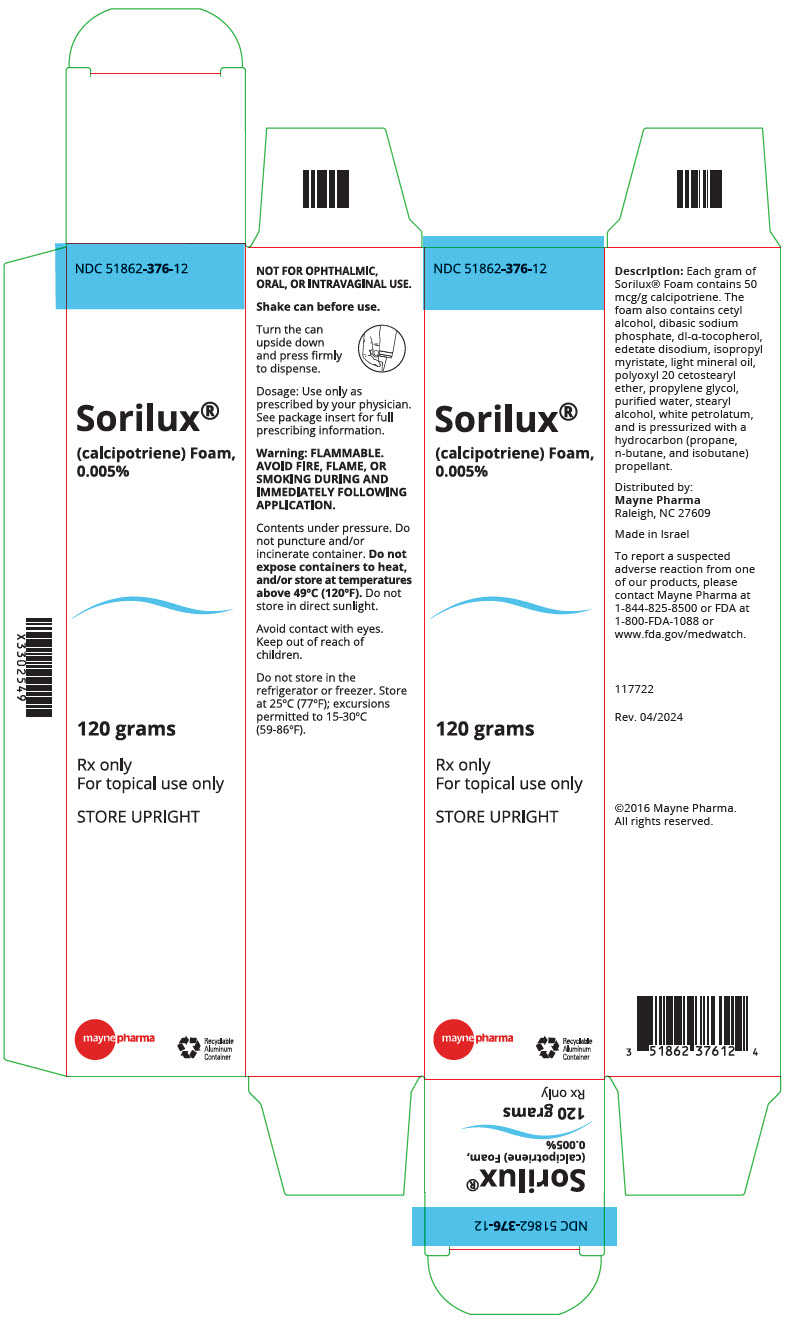 DRUG LABEL: SORILUX
NDC: 51862-376 | Form: AEROSOL, FOAM
Manufacturer: Mayne Pharma
Category: prescription | Type: HUMAN PRESCRIPTION DRUG LABEL
Date: 20240509

ACTIVE INGREDIENTS: calcipotriene 50 ug/1 g
INACTIVE INGREDIENTS: CETYL ALCOHOL; SODIUM PHOSPHATE, DIBASIC, UNSPECIFIED FORM; EDETATE DISODIUM; ISOPROPYL MYRISTATE; LIGHT MINERAL OIL; POLYOXYL 20 CETOSTEARYL ETHER; PROPYLENE GLYCOL; WATER; STEARYL ALCOHOL; .ALPHA.-TOCOPHEROL, DL-; PETROLATUM

HIGHLIGHTS OF PRESCRIBING INFORMATION

These highlights do not include all the information needed to use SORILUX safely and effectively. See full prescribing information for SORILUX.
SORILUX (calcipotriene) foam, for topical use
Initial U.S. Approval: 1993

RECENT MAJOR CHANGES

Indications and Usage (1) | 11/2019

1 INDICATIONS AND USAGE

SORILUX® Foam is a vitamin D analog indicated for the topical treatment of plaque psoriasis of the scalp and body in adults and pediatric patients 4 years of age and older. (1)

2 DOSAGE AND ADMINISTRATION

- For topical use only; not for oral, ophthalmic, or intravaginal use. (2)
- Apply twice daily. (2)

3 DOSAGE FORMS AND STRENGTHS

0.005%, foam. (3)

4 CONTRAINDICATIONS

- Do not use in patients with known hypercalcemia. (4)

5 WARNINGS AND PRECAUTIONS

- Flammability: Contents are flammable. Instruct the patient the avoid fire, flame, and smoking during and immediately following application. (5.1)
- Effects on Calcium Metabolism: If elevation of serum calcium occurs, instruct patients to discontinue treatment until normal calcium levels are restored. (5.2)

6 ADVERSE REACTIONS

Adverse reactions reported in ≥ 1% of subjects treated with SORILUX Foam and at a higher incidence than subjects treated with vehicle were application site erythema and application site pain. (6.1)

To report SUSPECTED ADVERSE REACTIONS, contact Mayne Pharma at 1-844-825-8500 or FDA at 1-800-FDA-1088 or www.fda.gov/medwatch. (6)

FULL PRESCRIBING INFORMATION

1 INDICATIONS AND USAGE

SORILUX Foam is indicated for the topical treatment of plaque psoriasis of the scalp and body in adults and pediatric patients 4 years of age and older.

2 DOSAGE AND ADMINISTRATION

SORILUX Foam is for topical use only. SORILUX Foam is not for oral, ophthalmic, or intravaginal use.

Apply a thin layer of SORILUX Foam twice daily to the affected areas and rub in gently and completely. Avoid contact with the face and eyes.

3 DOSAGE FORMS AND STRENGTHS

0.005%, white foam. SORILUX Foam contains calcipotriene 50 mcg/g in an aqueous-based emulsion foam vehicle.

4 CONTRAINDICATIONS

SORILUX Foam should not be used by patients with known hypercalcemia.

5 WARNINGS AND PRECAUTIONS

5.1 Flammability

The propellant in SORILUX Foam is flammable. Instruct the patient to avoid fire, flame, and smoking during and immediately following application.

5.2 Effects on Calcium Metabolism

Elevation of serum calcium has occurred with use of calcipotriene. If elevation in serum calcium outside the normal range should occur, discontinue treatment until normal calcium levels are restored.

6 ADVERSE REACTIONS

6.1 Clinical Trials Experience

Because clinical trials are conducted under widely varying conditions, adverse reaction rates observed in clinical trials of a drug cannot be directly compared with rates in the clinical trials of another drug and may not reflect the rates observed in clinical practice.

SORILUX Foam was studied in four vehicle-controlled trials. A total of 1094 adult subjects with plaque psoriasis, including 654 exposed to SORILUX Foam, were treated twice daily for 8 weeks. Adverse reactions reported in ≥1% of subjects treated with SORILUX Foam and at a higher incidence than subjects treated with vehicle were application site erythema (2%) and application site pain (3%). The incidence of these adverse reactions was similar between the body and scalp.

In an open-label study, 19 pediatric subjects age 12 to less than 17 years applied SORILUX Foam twice daily for 14 days and once on Day 15. Adverse reactions included application site pain, application site pruritus and pruritus [see Clinical Pharmacology (12.2 and 12.3) and Pediatric Use (8.4)].

In an open-label study, 36 pediatric subjects age 4 to less than 12 years applied SORILUX Foam twice daily for up to 8 weeks. Adverse reactions included application site pain and contact dermatitis [see Clinical Pharmacology (12.2 and 12.3) and Pediatric Use (8.4)].

6.2 Postmarketing Experience

The following adverse reactions have been identified during post approval use of SORILUX Foam. Because these reactions are reported voluntarily from a population of uncertain size, it is not always possible to reliably estimate their frequency or establish a causal relationship to drug exposure.

Skin and Subcutaneous: application site vesicles

8 USE IN SPECIFIC POPULATIONS

8.1 Pregnancy

Risk Summary

Although there are no available data on the drug- associated risk of major birth defects, miscarriage or adverse maternal or fetal outcomes in pregnant women exposed to SORILUX Foam, systemic exposure to calcipotriene is likely to be low [see Clinical Pharmacology (12.2, 12.3)].

In animal reproduction studies, oral administration of calcipotriene to pregnant rats and rabbits during the period of organogenesis resulted in an increased incidence of minor skeletal abnormalities, including enlarged fontanelles and extra ribs in rats and an increased incidence of minor skeletal abnormalities, including incomplete ossification of pubic bones and forelimb phalanges in rabbits (see Data). The available data do not allow the calculation of relevant comparisons between the systemic exposure of calcipotriene observed in animal studies to the systemic exposure that would be expected in humans after topical use of SORILUX Foam.

The estimated background risk of major birth defects and miscarriage for the indicated population is unknown. All pregnancies have a background risk of birth defect, loss, or other adverse outcomes. In the U.S. general population, the estimated risk of major birth defects and miscarriage in clinically recognized pregnancies is 2 to 4% and 15 to 20%, respectively.

Data

Animal Data

Embryofetal development studies were conducted with calcipotriene after oral administration in rats and rabbits. Pregnant rats received daily oral administration of calcipotriene during the period of organogenesis. Fetuses from dams dosed with 54 mcg/kg/day (318 mcg/m^2/day) exhibited a significantly increased incidence of minor skeletal abnormalities consisting primarily of enlarged fontanelles and extra ribs. The enlarged fontanelles are most likely due to calcipotriene's effect upon calcium metabolism. There were no effects on the incidence of major malformations in fetuses.

Pregnant rabbits received daily oral administration of calcipotriene during the period of organogenesis. Increased rabbit maternal and fetal toxicity was noted at 12 mcg/kg/day (132 mcg/m^2/day). Fetuses from does dosed with 36 mcg/kg/day (396 mcg/m^2/day) exhibited a significantly increased incidence of minor skeletal abnormalities including incomplete ossification of pubic bones and forelimb phalanges. There were no effects on the incidence of major malformations in fetuses.

8.2 Lactation

Risk Summary

There are no data on the presence of topically administered calcipotriene in human or animal milk, the effects on the breastfed infant, or the effects on milk production. After topical administration of SORILUX Foam, concentrations of calcipotriene in plasma are low, and therefore, concentrations in human milk are likely to be low [see Clinical Pharmacology (12.3)]. The developmental and health benefits of breastfeeding should be considered along with the mother's clinical need for and any potential adverse effects on the breastfed child from SORILUX Foam or from the underlying maternal condition.

8.4 Pediatric Use

The safety and effectiveness of SORILUX Foam have been established in pediatric patients age 4 years and older for topical treatment of plaque psoriasis of the scalp and body.

Use of SORILUX Foam in this age group is supported by two adequate and well controlled 8-week trials in adults and adolescents 12 years of age and older, with additional data from a 15-day open-label safety and pharmacokinetics (PK) study conducted in 19 subjects 12 to less than 17 years of age; and an 8-week open-label safety and PK study in 36 subjects 4 to 11 years of age with psoriasis. Data from 19 subjects aged 12 to less than 17 years and 18 subjects aged 5 to 11 years showed no significant effects on indices of calcium metabolism. Systemic concentrations of calcipotriene were not quantifiable in the two studies in subjects aged 7 years to less than 17 years. [see Clinical Studies (14), Clinical Pharmacology (12.2, 12.3) and Adverse Reactions (6.1)].

The safety and effectiveness of SORILUX Foam in pediatric patients less than 4 years of age have not been established.

8.5 Geriatric Use

Clinical trials of SORILUX Foam did not include sufficient numbers of subjects aged 65 years and over to determine whether they respond differently from younger subjects. Other reported clinical experience has not identified differences in responses between the elderly and younger patients.

10 OVERDOSAGE

Topically applied calcipotriene can be absorbed in sufficient amounts to produce systemic effects. Elevated serum calcium has been observed with use of topical calcipotriene [See Warnings and Precautions (5.2)].

11 DESCRIPTION

SORILUX Foam contains the compound calcipotriene, a synthetic vitamin D3 analog, in an aqueous-based emulsion foam vehicle for topical dermatologic use.

Chemically, calcipotriene is (5Z,7E,22E,24S)-24-cyclopropyl-9,10-secochola-5,7,10(19), 22-tetraene- 1α,3β,24-triol. The structural formula is represented below:

Molecular Formula: C27H40O3 Molecular Weight: 412.6

Calcipotriene is a white or off-white crystalline substance. SORILUX Foam contains calcipotriene 50 mcg/g in an aqueous-based emulsion foam vehicle consisting of cetyl alcohol, dibasic sodium phosphate, dl-α-tocopherol, edetate disodium, isopropyl myristate, light mineral oil, polyoxyl 20 cetostearyl ether, propylene glycol, purified water, stearyl alcohol, and white petrolatum. SORILUX Foam is dispensed from an aluminum can pressurized with a hydrocarbon (propane/n-butane/isobutane) propellant.

12 CLINICAL PHARMACOLOGY

12.1 Mechanism of Action

Calcipotriene is a synthetic vitamin D3 analog that has a similar receptor binding affinity as natural vitamin D3. However, the exact mechanism of action contributing to the clinical efficacy in the treatment of psoriasis is unknown.

12.2 Pharmacodynamics

Effects on Calcium Metabolism

In 19 subjects with psoriasis aged 12 to less than 17 years treated with SORILUX Foam two times a day for 15 days, there was no significant effect on indices of calcium metabolism including serum albumin adjusted calcium, urine calcium/creatinine ratio, iPTH, alkaline phosphatase, magnesium and phosphorus.

The effects of SORILUX Foam, 0.005%, on calcium metabolism were evaluated in 18 pediatric subjects 5 to 11 years of age receiving SORILUX Foam administered twice daily for a minimum of 14 days (mean: 56 days, range: 14 to 69 days). These subjects had plaque psoriasis involving an average of 10% of the body surface area (BSA) (range: 0.5%-36.5%). There was no relationship between urinary calcium/creatinine ratio (comparing Week 2 to Baseline) and % BSA treated.

12.3 Pharmacokinetics

The systemic absorption of calcipotriene in subjects with psoriasis of the body was evaluated at steady state following application of either SORILUX Foam or calcipotriene ointment to a body surface area of 5% to 10%. In the SORILUX Foam treatment group, 15 out of 16 subjects had calcipotriene plasma concentrations below the limit of quantitation (10 pg/mL), while in the calcipotriene ointment treated group, 5 out of 16 subjects had measurable calcipotriene plasma concentrations at various time points. All measurable plasma calcipotriene concentrations were below 25 pg/mL.

The pharmacokinetics of SORILUX Foam, 0.005% was investigated when applied topically for 15 days to 17 subjects aged 12 to less than 17 years with moderate plaque psoriasis involving a mean BSA of 24%, excluding face and scalp, and a mean scalp involvement of 43%. Systemic concentration of calcipotriene were not quantifiable in any of the subjects (limit of quantification = 10 pg/mL).

In 11 pediatric subjects 7 to 11 years of age with plaque psoriasis involving a mean BSA of 10%, plasma concentration of calcipotriene was measured following 2 weeks of twice daily administration of SORILUX Foam. No subject had quantifiable calcipotriene plasma concentration (limit of quantification = 10 pg/mL).

The systemic disposition of calcipotriene is expected to be similar to that of the naturally occurring vitamin D. Absorbed calcipotriene is known to be converted to inactive metabolites within 24 hours of application and the metabolism occurs via a similar pathway to the natural hormone.

13 NONCLINICAL TOXICOLOGY

13.1 Carcinogenesis, Mutagenesis, Impairment of Fertility

Calcipotriene topically administered to mice for up to 24 months at dose levels of 3, 10, or 30 mcg/kg/day (corresponding to 9, 30, or 90 mcg /m^2/day) showed no significant changes in tumor incidence when compared with controls.

The genotoxic potential of calcipotriene was evaluated in an Ames assay, a mouse lymphoma TK locus assay, a human lymphocyte chromosome aberration assay, and a mouse micronucleus assay. All assay results were negative.

Studies in rats at oral doses up to 54 mcg /kg/day (318 mcg /m^2/day) of calcipotriene indicated no impairment of fertility or general reproductive performance.

14 CLINICAL STUDIES

In two multi-center, randomized, double-blind, vehicle-controlled clinical trials a total of 659 subjects with psoriasis were randomized 2:1 to SORILUX Foam or vehicle; subjects applied the assigned treatment twice daily for 8 weeks. Baseline disease severity was graded using a 5-point Investigator Static Global Assessment scale (ISGA), on which subjects scored either "mild" or "moderate" as shown in Table 1.

Table 1. Investigator Static Global Assessment (ISGA) Scale for Body
Disease Severity | Grade | Definition
Clear | 0 | No evidence of scaling, erythema, or plaque thickness
Almost clear | 1 | Occasional fine scale, faint erythema, and barely perceptible plaque thickness
Mild | 2 | Fine scale with light coloration and mild plaque elevation
Moderate | 3 | Coarse scale with moderate red coloration and moderate plaque thickness
Severe | 4 | Thick tenacious scale with deep coloration and severe plaque thickness

Efficacy evaluation was carried out at Week 8 with treatment success being defined as a score of "clear" (grade 0) or "almost clear" (grade 1) and at least 2 grade improvement from the baseline score. Approximately 30% of enrolled subjects were graded as "mild" on the ISGA scale. The study population ranged in age from 12 to 89 years with 10 subjects less than 18 years of age at baseline. The subjects were 54% male and 88% Caucasian. Table 2 presents the efficacy results for each trial.

Table 2. Number and Percent of Subjects Achieving Success for Body at Week 8 in Each Trial
 | Trial 1 |  | Trial 2
 | SORILUX Foam N = 223 | Vehicle Foam N = 113 | SORILUX Foam N = 214 | Vehicle Foam N = 109
Number (%) of Subjects with Treatment Success | 31 (14%) | 8 (7%) | 58 (27%) | 17 (16%)

In one trial, subjects graded as "mild" at baseline showed a greater response to vehicle than SORILUX Foam.

Table 3 presents the success rates by disease severity at baseline for each trial.

Table 3. Number and Percent of Subjects Achieving Success for Body by Baseline ISGA Score and by Trial
 | Trial 1 |  | Trial 2
ISGA Scores at Baseline | SORILUX Foam (N = 223) | Vehicle Foam (N = 113) | SORILUX Foam (N = 214) | Vehicle Foam (N = 109)
Mild | 2/73 (2.7%) | 3/34 (8.8%) | 8/56 (14.3%) | 4/31 (12.9%)
Moderate | 29/150 (19.3%) | 5/79 (6.3%) | 50/158 (31.6%) | 13/78 (16.7%)

In another multi-center, randomized, double-blind, vehicle-controlled clinical trial, a total of 363 subjects with moderate plaque psoriasis of the scalp and body were randomized 1:1 to SORILUX Foam or vehicle. Subjects applied the assigned treatment to the affected areas twice daily for 8 weeks.

Baseline disease severity of the scalp was graded using a 6-point ISGA; a score of "moderate" corresponded to grade 3.

The primary efficacy evaluation for scalp involvement was carried out at Week 8 with treatment success being defined as a score of "clear" (grade 0) or "almost clear" (grade 1). The study population ranged in age from 12 to 97 years with 11 subjects less than 18 years of age at baseline. The subjects were 60% male and 87% Caucasian. Table 4 presents the efficacy results for the trial.

Table 4. Number and Percent of Subjects Achieving Success for Scalp at Week 8
 | Trial 3
 | SORILUX Foam N = 181 | Vehicle Foam N = 182
Number (%) of Subjects with Treatment Success | 74 (41%) | 44 (24%)

The contribution to efficacy of individual components of the vehicle has not been established.

16 HOW SUPPLIED/STORAGE AND HANDLING

16.1 How Supplied

SORILUX (calcipotriene) Foam, 0.005%, is supplied as follows:

120 g aluminum can | NDC 51862-376-12

16.2 Storage and Handling

- Store at 20ºC to 25°C (68°F to 77°F); excursions permitted to 15°C – 30°C (59°F – 86°F).
- Flammable. Contents under pressure. Do not puncture or incinerate. Do not expose to heat or store at temperatures above 120°F (49°C).
- Keep out of reach of children.

17 PATIENT COUNSELING INFORMATION

Advise the patient to read the FDA-approved patient labeling (Patient Information).

Inform the patient to adhere to the following instructions:

- Apply SORILUX Foam to the affected skin areas.
- Apply SORILUX Foam to the scalp when the hair is dry.
- Avoid fire, flame, and smoking during and immediately following application since SORILUX Foam is flammable.
- Avoid contact with the face and eyes. If SORILUX Foam gets on the face or in or near their eyes, rinse thoroughly with water.
- Talk to your doctor if your skin does not improve after treatment with SORILUX Foam for 8 weeks.
- Wash your hands after applying SORILUX Foam unless your hands are the affected site.
- Do not place SORILUX Foam in the refrigerator or freezer.

SORILUX is a registered trademark of Mayne Pharma LLC.

Distributed by:
Mayne Pharma
Raleigh, NC 27609
141294

Patient Information
SORILUX (SOR-i-lux)
(calcipotriene)
Foam, 0.005%

Important: SORILUX Foam is for use on the skin only (topical use). Do not use SORILUX Foam in your mouth, eyes, or vagina.

WHAT IS SORILUX FOAM?
SORILUX Foam is a prescription medicine used on the skin (topical) to treat plaque psoriasis of the scalp and body in people 4 years of age and older.
It is not known if SORILUX Foam is safe and effective in people under 4 years old.

Do not use SORILUX Foam if you have been told by your healthcare provider that you have a high level of calcium in your blood (hypercalcemia).

BEFORE USING SORILUX FOAM, TELL YOUR HEALTHCARE PROVIDER ABOUT ALL YOUR MEDICAL CONDITIONS, INCLUDING IF YOU:

- are pregnant or planning to become pregnant. It is not known if SORILUX Foam will harm your unborn baby.
- are breastfeeding or plan to breastfeed. It is not known if SORILUX Foam passes into your breast milk. Talk to your healthcare provider about the best way to feed your baby during treatment with SORILUX Foam.

Tell your healthcare provider about all the medicines you take, including prescription and over-the-counter medicines, vitamins, and herbal supplements.
Know the medicines you take. Keep a list of your medicines with you to show your healthcare provider and pharmacist when you get a new medicine.

HOW SHOULD I USE SORILUX FOAM?

- Use SORILUX Foam exactly as your healthcare provider tells you to use it. See the detailed "Instructions for Use" at the end of this leaflet for directions about how to apply SORILUX Foam the right away.
- SORILUX Foam is usually applied to the affected skin areas 2 times each day.
- For your scalp, apply SORILUX Foam when your hair is dry.
- Talk with your healthcare provider if your skin does not improve after 8 weeks of treatment with SORILUX Foam.
- Wash your hands after applying SORILUX Foam unless you are using the medicine to treat your hands.

WHAT SHOULD I AVOID WHILE USING SORILUX FOAM?

- SORILUX Foam is flammable. Avoid fire, flame, and smoking during and right after you apply SORILUX Foam.
- Avoid getting SORILUX Foam on your face or in or near your eyes. If SORILUX Foam gets on your face or in your eyes, rinse well with water.

WHAT ARE THE POSSIBLE SIDE EFFECTS OF SORILUX FOAM?
SORILUX Foam may cause serious side effects, including:

- Too much calcium in your blood. Your healthcare provider may tell you to stop using SORILUX Foam until your calcium levels become normal.

The most common side effects of SORILUX Foam include redness and pain of the treated skin areas.
These are not all the possible side effects of SORILUX Foam.
Call your doctor for medical advice about side effects. You may report side effects to FDA at 1-800-FDA-1088.
You may also report side effects to Mayne Pharma at 1-844-825-8500.

HOW SHOULD I STORE SORILUX FOAM?

- Store SORILUX Foam at room temperature, between 68°F to 77°F (20C° to 25°C).
- Do not store SORILUX Foam in the refrigerator or freezer.
- Do not expose SORILUX Foam to heat or store at temperatures above 120°F (49°C).
- Do not puncture or burn the SORILUX Foam can.

Keep SORILUX Foam and all medicines out of the reach of children.

GENERAL INFORMATION ABOUT THE SAFE AND EFFECTIVE USE OF SORILUX FOAM.
Medicines are sometimes prescribed for purposes other than those listed in a Patient Information leaflet. Do not use SORILUX Foam for a condition for which it was not prescribed. Do not give SORILUX Foam to other people even if they have the same symptoms you have. It may harm them. You can ask your healthcare provider or pharmacist for information about SORILUX Foam that is written for health professionals.

WHAT ARE THE INGREDIENTS IN SORILUX FOAM?
Active ingredient: calcipotriene
Inactive ingredients: cetyl alcohol, dibasic sodium phosphate, dl-α-tocopherol, edetate disodium, isopropyl myristate, light mineral oil, polyoxyl 20 cetostearyl ether, propylene glycol, purified water, stearyl alcohol, and white petrolatum. The foam is dispensed from an aluminum can pressurized with a hydrocarbon (propane/n-butane/isobutane) propellant.
Distributed by:
Mayne Pharma
Raleigh, NC 27609
SORILUX is a registered trademark of Mayne Pharma LLC.

This Patient Information has been approved by the U.S. Food and Drug Administration.

Revised: 04/2024

Instructions for Use SORILUX (SOR-i-lux) (calcipotriene) Foam, 0.005%

Read this Instructions for Use before you start using SORILUX Foam and each time you get a refill. There may be new information. This information does not take the place of talking with your healthcare provider about your medical condition or treatment.

Important Information:

- SORILUX Foam is for use on the skin only (topical use). Do not use SORILUX Foam in your mouth, eyes, or vagina.
- Avoid getting SORILUX Foam on your face or in your eyes. If you accidentally get SORILUX Foam on your face or in your eyes, rinse well with water.

How to apply SORILUX Foam to your body:

Follow your healthcare providers instructions on how much SORILUX Foam to use and where to use it. Wash your hands after applying SORILUX Foam unless you are treating areas on your hands.

Step 1. Before applying SORILUX Foam for the first time, break the tiny plastic piece at the base of the can's rim by gently pushing back (away from the piece) on the nozzle. See Figure A.

Figure A

Step 2: Shake the can of SORILUX Foam before use. See Figure B.

Figure B

Step 3: Turn the can of SORILUX Foam upside down and press the nozzle. See Figure C.

Figure C

Step 4. Dispense a small amount of SORILUX Foam into the palm of your hand. See Figure D.

Figure D

Step 5. Use enough SORILUX Foam to cover the affected area with a thin layer. Gently rub the foam into the affected area until it disappears into the skin. See Figures E and F

Figure E

Figure F

How to apply SORILUX Foam to your scalp:

Step 6. Apply SORILUX Foam to your scalp when your hair is dry. Part your hair and apply directly on the affected area. See Figure G. Wash your hands after applying SORILUX Foam.

Figure G

This Instructions for Use has been approved by the U.S. Food and Drug Administration.

Distributed by: Mayne Pharma, Raleigh, NC 27609

Revised: 04/2024

PRINCIPAL DISPLAY PANEL - 120 gram Can Carton

NDC 51862-376-12

Sorilux®

(calcipotriene) Foam,
0.005%

120 grams

Rx only
For topical use only

STORE UPRIGHT

mayne pharma

Recyclable
Aluminum
Container